DRUG LABEL: Unknown
Manufacturer: ESP Pharma, Inc.
Category: prescription | Type: Human Prescription Drug Label
Date: 20070514

IV Busulfex
(busulfan) Injection

Caution: Must be diluted prior to use.

Rx only

WARNING

BUSULFEX® (busulfan) Injection is a potent cytotoxic drug that causes profound myelosuppression at the recommended dosage. It should be administered under the supervision of a qualified physician who is experienced in allogeneic hematopoietic stem cell transplantation, the use of cancer chemotherapeutic drugs and the management of patients with severe pancytopenia. Appropriate management of therapy and complications is only possible when adequate diagnostic and treatment facilities are readily available. SEE “WARNINGS” SECTION FOR INFORMATION REGARDING BUSULFAN-INDUCED PANCYTOPENIA IN HUMANS.

DESCRIPTION

Busulfan is a bifunctional alkylating agent known chemically as 1,4- butanediol, dimethanesulfonate. BUSULFEX® (busulfan) Injection is intended for intravenous administration. It is supplied as a clear, colorless, sterile, solution in 10 mL single use vials.

Each vial of BUSULFEX contains 60 mg (6 mg/mL) of busulfan, the active ingredient, a white crystalline powder with a molecular formula of CH3SO2O(CH2)4OSO2CH3 and a molecular weight of 246 g/mole. Busulfan is dissolved in N,N-dimethylacetamide (DMA) 33% vol/vol and Polyethylene Glycol 400, 67% vol/vol. The solubility of busulfan in water is 0.1 g/L and the pH of BUSULFEX diluted to approximately 0.5 mg/mL busulfan in 0.9% Sodium Chloride Injection, USP or 5% Dextrose Injection, USP as recommended for infusion reflects the pH of the diluent used and ranges from 3.4 to 3.9.

BUSULFEX is intended for dilution with 0.9% Sodium Chloride Injection, USP or 5% Dextrose Injection, USP prior to intravenous infusion.

CLINICAL PHARMACOLOGY

Mechanism of Action

Busulfan is a bifunctional alkylating agent in which two labile methanesulfonate groups are attached to opposite ends of a four-carbon alkyl chain. In aqueous media, busulfan hydrolyzes to release the methanesulfonate groups. This produces reactive carbonium ions that can alkylate DNA. DNA damage is thought to be responsible for much of the cytotoxicity of busulfan.

Pharmacokinetics

The pharmacokinetics of BUSULFEX were studied in 59 patients participating in a prospective trial of a BUSULFEX-cyclophosphamide preparatory regimen prior to allogeneic hematopoietic progenitor stem cell transplantation. Patients received 0.8 mg/kg BUSULFEX every six hours, for a total of 16 doses over four days. Fifty-five of fifty-nine patients (93%) administered BUSULFEX maintained AUC values below the target value (<1500 µM•min).

Table 1: Steady State Pharmacokinetic Parameters Following Busulfex ® (busulfan) Infusion (0.8 mg/kg; N=59)
 | Mean | CV (%) | Range
Cmax (ng/mL) | 1222 | 18 | 496-1684
AUC (μM•min) | 1167 | 20 | 556-1673
CL (ml/min/kg)* | 2.52 | 25 | 1.49-4.31
* Clearance normalized to actual body weight for all patients.

BUSULFEX pharmacokinetics showed consistency between dose 9 and dose 13 as demonstrated by reproducibility of steady state Cmax and a low coefficient of variation for this parameter.

In a pharmacokinetic study of BUSULFEX in 24 pediatric patients, the population pharmacokinetic (PPK) estimates of BUSULFEX for clearance (CL) and volume of distribution (V) were determined. For actual body weight, PPK estimates of CL and V were 4.04 L/hr/20 kg (3.37 ml/min/kg; interpatient variability 23%); and 12.8 L/20 kg (0.64 L/kg; interpatient variability 11%).

Distribution, Metabolism, Excretion:

Studies of distribution, metabolism, and elimination of BUSULFEX have not been done; however, the literature on oral busulfan is relevant. Additionally, for modulating effects on pharmacodynamic parameters see Drug Interactions.

Distribution:Busulfan achieves concentrations in the cerebrospinal fluid approximately equal to those in plasma. Irreversible binding to plasma elements, primarily albumin, has been estimated to be 32.4 ± 2.2% which is consistent with the reactive electrophilic properties of busulfan.

Metabolism:Busulfan is predominantly metabolized by conjugation with glutathione, both spontaneously and by glutathione S-transferase (GST) catalysis. This conjugate undergoes further extensive oxidative metabolism in the liver.

Excretion:Following administration of ^14C- labeled busulfan to humans, approximately 30% of the radioactivity was excreted into the urine over 48 hours; negligible amounts were recovered in feces. The incomplete recovery of radioactivity may be due to the formation of long-lived metabolites or due to nonspecific alkylation of macromolecules.

CLINICAL STUDIES

Documentation of the safety and efficacy of busulfan as a component of a conditioning regimen prior to allogeneic hematopoietic progenitor cell reconstitution is derived from two sources: i) analysis of a prospective clinical trial of BUSULFEX that involved 61 patients diagnosed with various hematologic malignancies, and ii) the published reports of randomized, controlled trials that employed high-dose oral busulfan as a component of a conditioning regimen for transplantation, which were identified in a literature review of five established commercial databases.

The prospective trial was a single-arm, open-label study in 61 patients who received BUSULFEX as part of a conditioning regimen for allogeneic hematopoietic stem cell transplantation. The study included patients with acute leukemia past first remission (first or subsequent relapse), with high-risk first remission, or with induction failure; chronic myelogenous leukemia (CML) in chronic phase, accelerated phase, or blast crisis; primary refractory or resistant relapsed Hodgkin’s disease or non-Hodgkin’s lymphoma; and myelodysplastic syndrome. Forty-eight percent of patients (29/61) were heavily pretreated, defined as having at least one of the following: prior radiation, ≥3 prior chemotherapeutic regimens, or prior hematopoietic stem cell transplant. Seventy-five percent of patients (46/61) were transplanted with active disease.

Patients received 16 BUSULFEX doses of 0.8 mg/kg every 6 hours as a two-hour infusion for 4 days, followed by cyclophosphamide 60 mg/kg once per day for two days (BuCy2 regimen). All patients received 100% of their scheduled BUSULFEX regimen. No dose adjustments were made. After one rest day, allogeneic hematopoietic progenitor cells were infused. The efficacy parameters in this study were myeloablation (defined as one or more of the following: absolute neutrophil count [ANC] less than 0.5x10^9/L, absolute lymphocyte count [ALC] less than 0.1x10^9/L, thrombocytopenia defined as a platelet count less than 20,000/mm3 or a platelet transfusion requirement) and engraftment (ANC≥0.5x10^9/L).

All patients (61/61) experienced myeloablation. The median time to neutropenia was 4 days. All evaluable patients (60/60) engrafted at a median of 13 days post-transplant (range 9 to 29 days); one patient was considered non-evaluable because he died of a fungal pneumonia 20 days after BMT and before engraftment occurred. All but 13 of the patients were treated with prophylactic G-CSF. Evidence of donor cell engraftment and chimerism was documented in all patients who had a chromosomal sex marker or leukemic marker (43/43), and no patient with chimeric evidence of allogeneic engraftment suffered a later loss of the allogeneic graft. There were no reports of graft failure in the overall study population. The median number of platelet transfusions per patient was 6, and the median number of red blood cell transfusions per patient was 4.

Twenty-three patients (38%) relapsed at a median of 183 days post-transplant (range 36 to 406 days). Sixty-two percent of patients (38/61) were free from disease with a median follow-up of 269 days post-transplant (range 20 to 583 days). Forty-three patients (70%) were alive with a median follow up of 288 days post-transplant (range 51 to 583 days). There were two deaths before BMT Day +28 and six additional patients died by BMT Day +100. Ten patients (16%) died after BMT Day +100, at a median of 199 days post-transplant (range 113 to 275 days).

Oral Busulfan Literature Review.Four publications of randomized, controlled trials that evaluated a high-dose oral busulfan-containing conditioning regimen (busulfan 4 mg/kg/d x 4 days + cyclophosphamide 60 mg/kg/d x 2 days) for allogeneic transplantation in the setting of CML were identified. Two of the studies (Clift and Devergie) had populations confined to CML in chronic phase that were randomized between conditioning with busulfan/cyclophosphamide (BU/CY) and cyclophosphamide/total body irradiation (CY/TBI). A total of 138 patients were treated with BU/CY in these studies. The populations of the two remaining studies (Ringden and Blume) included patients with CML, acute lymphoblastic leukemia (ALL), and acute myelogenous leukemia (AML). In the Nordic BMT Group study published by Ringden, et al., 57 patients had CML, and of those, 30 were treated with BU/CY. Patients with CML in chronic phase, accelerated phase, and blast crisis were eligible for this study. The participants with CML (34/122 patients) in a SWOG study published by Blume, et al., had disease beyond first chronic phase. Twenty of those CML patients were treated with BU/CY, and the TBI comparator arm utilized etoposide instead of cyclophosphamide.

Table 2 below summarizes the efficacy analyses reported from these 4 studies.

Table 2: Summary of efficacy analyses from the randomized, controlled trials utilizing a high dose oral busulfan-containing conditioning regimen identified in a literature review.
Clift, 1994
CML Chronic Phase;
3 year Overall |  | 3 year DFS |  | Relapse |  | Time to Engraftment
Survival |  | (p=0.43) |  |  |  | (ANC ≥ 500)
BU/CY | CY/TBI | BU/CY | CY/TBI | BU/CY | CY/TBI | BU/CY | CY/TBI
80% | 80% | 71% | 68% | 13% | 13% | 22.6 days | 22.3 days
Devergie, 1995
CML Chronic Phase;
5 year Overall Survival |  | 5 year DFS (p=0.75) |  | Relapse (Relative Risk analysis |  | Time to Engraftment (ANC ≥ 500)
(p=0.5) |  |  |  | BU/CY:CY/TBI)
 |  |  |  | (p=0.04)
BU/CY | CY/TBI | BU/CY | CY/TBI | BU/CY | CY/TBI | BU/CY | CY/TBI
60.6% | 65.8% | 59.1% | 51.0% | 4.10 |  | None | None
±11.7% | ±12.5% | ±11.8% | ±14% | (95%CI =1.00-20.28) |  | Given | Given
Ringden, 1994
CML, AML, ALL;
3 year Overall |  | 3 year Relapse Free |  | Relapse |  | Time to Engraftment
Survival |  | Survival |  | (p=0.9) |  | (ANC >500)
(p<0.03) |  | (p=0.065)
BU/CY | CY/TBI | BU/CY | CY/TBI | BU/CY | CY/TBI | BU/CY | CY/TBI
62% | 76% | 56% | 67% | 22% | 26% | 20 days | 20 days
Blume, 1993*
CML, AML, ALL; Relative Risk Analysis BU/CY: Etoposide/TBI
RR of Mortality |  | DFS |  | RR of Relapse |  | Time to Engraftment
 |  |  |  | (Relative Risk analysis
 |  |  |  | BU/CY:Eto/TBI)
BU/CY | Eto/TBI | BU/CY | Eto/TBI | BU/CY | Eto/TBI | BU/CY | Eto/TBI
0.97 |  | Not Given |  | 1.02 |  | Not Given
(95% CI=0.64-1.48) |  |  |  | (95% CI=0.56-1.86)
*Eto = etoposide. TBI was combined with etoposide in the comparator arm of this study.
BU = Busulfan
CY = Cyclophosphamide
TBI = Total Body Irradiation
DFS = Disease Free Survival
ANC = Absolute Neutrophil Count

INDICATIONS AND USAGE

BUSULFEX® (busulfan) Injection is indicated for use in combination with cyclophosphamide as a conditioning regimen prior to allogeneic hematopoietic progenitor cell transplantation for chronic myelogenous leukemia.

CONTRAINDICATIONS

BUSULFEX is contraindicated in patients with a history of hypersensitivity to any of its components.

WARNINGS

BUSULFEX should be administered under the supervision of a qualified physician experienced in hematopoietic stem cell transplantation. Appropriate management of complications arising from its administration is possible only when adequate diagnostic and treatment facilities are readily available.

The following warnings pertain to different physiologic effects of BUSULFEX in the setting of allogeneic transplantation.

Hematologic:The most frequent serious consequence of treatment with BUSULFEX at the recommended dose and schedule is profound myelosuppression, occurring in all patients. Severe granulocytopenia, thrombocytopenia, anemia, or any combination thereof may develop. Frequent complete blood counts, including white blood cell differentials, and quantitative platelet counts should be monitored during treatment and until recovery is achieved. Absolute neutrophil counts dropped below 0.5x10^9/L at a median of 4 days post-transplant in 100% of patients treated in the BUSULFEX clinical trial. The absolute neutrophil count recovered at a median of 13 days following allogeneic transplantation when prophylactic G-CSF was used in the majority of patients. Thrombocytopenia (<25,000/mm^3 or requiring platelet transfusion) occurred at a median of 5-6 days in 98% of patients. Anemia (hemoglobin <8.0 g/dL) occurred in 69% of patients. Antibiotic therapy and platelet and red blood cell support should be used when medically indicated.

Neurological:Seizures have been reported in patients receiving highdose oral busulfan at doses producing plasma drug levels similar to those achieved following the recommended dosage of BUSULFEX. Despite prophylactic therapy with phenytoin, one seizure (1/42 patients) was reported during an autologous transplantation clinical trial of BUSULFEX. This episode occurred during the cyclophosphamide portion of the conditioning regimen, 36 hours after the last BUSULFEX dose. Anti-convulsant prophylactic therapy should be initiated prior to BUSULFEX treatment. Caution should be exercised when administering the recommended dose of BUSULFEX to patients with a history of a seizure disorder or head trauma or who are receiving other potentially epileptogenic drugs.

Hepatic:Current literature suggests that high busulfan area under the plasma concentration verses time curve (AUC) values (>1,500 µM•min) may be associated with an increased risk of developing hepatic venoocclusive disease (HVOD). Patients who have received prior radiation therapy, greater than or equal to three cycles of chemotherapy, or a prior progenitor cell transplant may be at an increased risk of developing HVOD with the recommended BUSULFEX dose and regimen. Based on clinical examination and laboratory findings, hepatic veno-occlusive disease was diagnosed in 8% (5/61) of patients treated with BUSULFEX in the setting of allogeneic transplantation, was fatal in 2/5 cases (40%), and yielded an overall mortality from HVOD in the entire study population of 2/61 (3%). Three of the five patients diagnosed with HVOD were retrospectively found to meet the Jones’ criteria. The incidence of HVOD reported in the literature from the randomized, controlled trials (see CLINICAL STUDIES) was 7.7%-12%.

Cardiac:Cardiac tamponade has been reported in pediatric patients with thalassemia (8/400 or 2% in one series) who received high doses of oral busulfan and cyclophosphamide as the preparatory regimen for hematopoietic progenitor cell transplantation. Six of the eight children died and two were saved by rapid pericardiocentesis. Abdominal pain and vomiting preceded the tamponade in most patients. No patients treated in the BUSULFEX (busulfan) Injection clinical trials experienced cardiac tamponade.

Pulmonary:Bronchopulmonary dysplasia with pulmonary fibrosis is a rare but serious complication following chronic busulfan therapy. The average onset of symptoms is 4 years after therapy (range 4 months to 10 years).

Carcinogenicity, Mutagenicity, Impairment of Fertility

Busulfan is a mutagen and a clastogen. In in vitro tests it caused mutations in Salmonella typhimuriumand Drosophila melanogaster. Chromosomal aberrations induced by busulfan have been reported in vivo(rats, mice, hamsters, and humans) and in vitro (rodent and human cells). The intravenous administration of busulfan (48 mg/kg given as biweekly doses of 12 mg/kg, or 30% of the total BUSULFEX dose on a mg/m^2 basis) has been shown to increase the incidence of thymic and ovarian tumors in mice. Four cases of acute leukemia occurred among 19 patients who became pancytopenic in a 243 patient study incorporating busulfan as adjuvant therapy following surgical resection of bronchogenic carcinoma. Clinical appearance of leukemia was observed 5-8 years following oral busulfan treatment. Busulfan is a presumed human carcinogen.

Ovarian suppression and amenorrhea commonly occur in premenopausal women undergoing chronic, low-dose busulfan therapy for chronic myelogenous leukemia. Busulfan depleted oocytes of female rats. Busulfan induced sterility in male rats and hamsters. Sterility, azoospermia and testicular atrophy have been reported in male patients.

The solvent DMA may also impair fertility. A DMA daily dose of 0.45 g/kg/d given to rats for nine days (equivalent to 44% of the daily dose of DMA contained in the recommended dose of BUSULFEX on a mg/m^2 basis) significantly decreased spermatogenesis in rats. A single sc dose of 2.2 g/kg (27% of the total DMA dose contained in BUSULFEX on a mg/m^2 basis) four days after insemination terminated pregnancy in 100% of tested hamsters.

Pregnancy

Busulfan may cause fetal harm when administered to a pregnant woman. Busulfan produced teratogenic changes in the offspring of mice, rats and rabbits when given during gestation. Malformations and anomalies included significant alterations in the musculoskeletal system, body weight gain, and size. In pregnant rats, busulfan produced sterility in both male and female offspring due to the absence of germinal cells in the testes and ovaries. The solvent, DMA, may also cause fetal harm when administered to a pregnant woman. In rats, DMA doses of 400 mg/kg/d (about 40% of the daily dose of DMA in the BUSULFEX dose on a mg/m^2 basis) given during organogenesis caused significant developmental anomalies. The most striking abnormalities included anasarca, cleft palate, vertebral anomalies, rib anomalies, and serious anomalies of the vessels of the heart. There are no adequate and well-controlled studies of either busulfan or DMA in pregnant women. If BUSULFEX is used during pregnancy, or if the patient becomes pregnant while receiving BUSULFEX, the patient should be apprised of the potential hazard to the fetus. Women of childbearing potential should be advised to avoid becoming pregnant.

PRECAUTIONS

Hematologic

At the recommended dosage of BUSULFEX (busulfan) Injection, profound myelosuppression is universal, and can manifest as neutropenia, thrombocytopenia, anemia, or a combination thereof. Patients should be monitored for signs of local or systemic infection or bleeding. Their hematologic status should be evaluated frequently.

Information for Patients

The increased risk of a second malignancy should be explained to the patient.

Laboratory Tests

Patients receiving BUSULFEX should be monitored daily with a complete blood count, including differential count and quantitative platelet count, until engraftment has been demonstrated.

To detect hepatotoxicity, which may herald the onset of hepatic venoocclusive disease, serum transaminases, alkaline phosphatase, and bilirubin should be evaluated daily through BMT Day +28.

Drug Interactions

Itraconazole decreases busulfan clearance by up to 25%, and may produce an AUC > 1500 µM•min in some patients. Fluconazole, and the 5-HT3 antiemetics odansetron (Zofran®) and granisetron (Kytril®) have all been used with BUSULFEX.

Phenytoin increases the clearance of busulfan by 15% or more, possibly due to the induction of glutathione-S-transferase. Since the pharmacokinetics of BUSULFEX were studied in patients treated with phenytoin, the clearance of BUSULFEX at the recommended dose may be lower and exposure (AUC) higher in patients not treated with phenytoin. Because busulfan is eliminated from the body via conjugation with glutathione, use of acetaminophen prior to (<72 hours) or concurrent with BUSULFEX may result in reduced busulfan clearance based upon the known property of acetaminophen to decrease glutathione levels in the blood and tissues.

Pregnancy

Pregnancy Category D. See WARNINGS.

Nursing Mothers

It is not known whether this drug is excreted in human milk. Because many drugs are excreted in human milk and because of the potential for tumorgenicity shown for busulfan in human and animal studies, a decision should be made whether to discontinue nursing or to discontinue the drug, taking into account the importance of the drug to the mother.

Special Populations

Pediatric:The effectiveness of BUSULFEX in the treatment of CML has not been specifically studied in pediatric patients. An open-label, uncontrolled study evaluated the pharmacokinetics of BUSULFEX in 24 pediatric patients receiving BUSULFEX as part of a conditioning regimen administered prior to hematopoietic progenitor cell transplantation for a variety of malignant hematologic (N=15) or non-malignant diseases (N=9). Patients ranged in age from 5 months to 16 years (median 3 years). BUSULFEX dosing was targeted to achieve an area under the plasma concentration curve (AUC) of 900-1350 µM•min with an initial dose of 0.8 mg/kg or 1.0 mg/kg (based on ABW) if the patient was >4 or ≤4 years, respectively. The dose was adjusted based on plasma concentration after completion of dose 1.

Patients received BUSULFEX doses every six hours as a two-hour infusion over four days for a total of 16 doses, followed by cyclophosphamide 50 mg/kg once daily for four days. After one rest day, hematopoietic progenitor cells were infused. All patients received phenytoin as seizure prophylaxis. The target AUC (900-1350 ± 5% µM•min) for BUSULFEX was achieved at dose 1 in 71% (17/24) of patients. Steady state pharmacokinetic testing was performed at dose 9 and 13. BUSULFEX levels were within the target range for 21 of 23 evaluable patients.

All 24 patients experienced neutropenia (absolute neutrophil count <0.5 x 10^9/L) and thrombocytopenia (platelet transfusions or platelet count <20,000/mm^3). Seventy-nine percent (19/24) of patients experienced lymphopenia (absolute lymphocyte count <0.1 x 10^9). In 23 patients, the ANC recovered to >0.5 x 10^9/L (median time to recovery = BMT day +13; range = BMT day +9 to +22). One patient who died on day +20 had not recovered to an ANC > 0.5 x 10^9/L.

Four (17%) patients died during the study. Two patients died within 28 days of transplant; one with pneumonia and capillary leak syndrome, and the other with pneumonia and veno-occlusive disease. Two patients died prior to day 100; one due to progressive disease and one due to multi-organ failure.

Adverse events were reported in all 24 patients during the study period (BMT day -10 through BMT day +28) or post-study surveillance period (day +29 through +100). These included vomiting (100%), nausea (83%), stomatitis (79%), hepatic veno-occlusive disease (HVOD) (21%), graft-versus host disease (GVHD) (25%), and pneumonia (21%).

Based on the results of this 24-patient clinical trial, a suggested dosing regimen of BUSULFEX in pediatric patients is shown in the following dosing nomogram:

BUSULFEX Dosing Nomogram
Patient’s Actual | BUSULFEX
Body Weight (ABW) | Dosage
≤12 kgs | 1.1 (mg/kg)
>12 kgs | 0.8 (mg/kg)

Simulations based on a pediatric population pharmacokinetic model indicate that approximately 60% of pediatric patients will achieve a target BUSULFEX exposure (AUC) between 900 to 1350 µM•min with the first dose of BUSULFEX using this dosing nomogram. Therapeutic drug monitoring and dose adjustment following the first dose of BUSULFEX is recommended.

Dose Adjustment Based on Therapeutic Drug Monitoring

Instructions for measuring the AUC of busulfan at dose 1 (see Blood Sample Collection for AUC Determination), and the formula for adjustment of subsequent doses to achieve the desired target AUC (1125 µM•min), are provided below.

Adjusted dose (mg) = Actual Dose (mg) x Target AUC (µM•min)/Actual AUC (µM•min)

For example, if a patient received a dose of 11 mg busulfan and if the corresponding AUC measured was 800 µM•min, for a target AUC of 1125 µM•min, the target mg dose would be:

Mg dose = 11 mg x 1125 µM•min / 800 µM•min = 15.5 mg

Busulfex dose adjustment may be made using this formula and instructions below.

Blood Sample Collection for AUC Determination:

Calculate the AUC (µM•min) based on blood samples collected at the following time points:

For dose 1: 2 hr (end of infusion), 4 hr and 6 hr (immediately prior to the next scheduled BUSULFEX administration). Actual sampling times should be recorded.

For doses other than dose 1: Pre-infusion (baseline), 2 hr (end of infusion), 4 hr and 6 hr (immediately prior to the next scheduled BUSULFEX administration).

AUC calculations based on fewer than the three specified samples may result in inaccurate AUC determinations.

For each scheduled blood sample, collect one to three mL of blood into heparinized (Na or Li heparin) Vacutainer® tubes. The blood samples should be placed on wet ice immediately after collection and should be centrifuged (at 4°C) within one hour. The plasma, harvested into appropriate cryovial storage tubes, is to be frozen immediately at -20°C. All plasma samples are to be sent in a frozen state (i.e., on dry ice) to the assay laboratory for the determination of plasma busulfan concentrations.

Calculation of AUC:

BUSULFEX AUC calculations may be made using the following instructions and appropriate standard pharmacokinetic formula:

Dose 1 AUCinfinity Calculation: AUCinfinity= AUC0-6hr+ AUCextrapolated,

where AUC0-6hr is to be estimated using the linear trapezoidal rule and AUC extrapolated can be computed by taking the ratio of the busulfan concentration at Hour 6 and the terminal elimination rate constant, z. The z must be calculated from the terminal elimination phase of the busulfan concentration vs. time curve. A “0” pre-dose busulfan concentration should be assumed, and used in the calculation of AUC.

If the AUC is assessed subsequent to Dose 1, steady-state AUCss (AUC0-6hr) is to be estimated from the trough, 2 hr, 4 hr and 6 hr concentrations using the linear trapezoidal rule.

Instructions for Drug Administration and Blood Sample Collection for Therapeutic Drug Monitoring:

An administration set with minimal residual hold up (priming) volume (1-3 mL) should be used for drug infusion to ensure accurate delivery of the entire prescribed dose and to ensure accurate collection of blood samples for therapeutic drug monitoring and dose adjustment.

Prime the administration set tubing with drug solution to allow accurate documentation of the start time of BUSULFEX infusion. Collect the blood sample from a peripheral IV line to avoid contamination with infusing drug. If the blood sample is taken directly from the existing central venous catheter (CVC), DO NOT COLLECT THE BLOOD SAMPLE WHILE THE DRUG IS INFUSINGto ensure that the end of infusion sample is not contaminated with any residual drug. At the end of infusion (2 hr), disconnect the administration tubing and flush the CVC line with 5 cc of normal saline prior to the collection of the end of infusion sample from the CVC port. Collect the blood samples from a different port than that used for the BUSULFEX infusion. When recording the BUSULFEX infusion stop time, do not include the time required to flush the indwelling catheter line. Discard the administration tubing at the end of the two-hour infusion.

See Preparation for Intravenous Administration section for detailed instructions on drug preparation.

Geriatric:Five of sixty-one patients treated in the BUSULFEX clinical trial were over the age of 55 (range 57-64). All achieved myeloablation and engraftment.

Gender, Race:Adjusting BUSULFEX dosage based on gender or race has not been adequately studied.

Renal Insufficiency:BUSULFEX has not been studied in patients with renal impairment.

Hepatic Insufficiency:BUSULFEX has not been administered to patients with hepatic insufficiency.

Other:Busulfan may cause cellular dysplasia in many organs. Cytologic abnormalities characterized by giant, hyperchromatic nuclei have been reported in lymph nodes, pancreas, thyroid, adrenal glands, liver, lungs and bone marrow. This cytologic dysplasia may be severe enough to cause difficulty in the interpretation of exfoliative cytologic examinations of the lungs, bladder, breast and the uterine cervix.

ADVERSE REACTIONS

Dimethylacetamide (DMA), the solvent used in the BUSULFEX formulation, was studied in 1962 as a potential cancer chemotherapy drug. In a Phase 1 trial, the maximum tolerated dose (MTD) was 14.8 g/m^2/d for four days. The daily recommended dose of BUSULFEX contains DMA equivalent to 42% of the MTD on a mg/m^2 basis. The dose-limiting toxicities in the Phase 1 study were hepatotoxicity as evidenced by increased liver transaminase (SGOT) levels and neurological symptoms as evidenced by hallucinations. The hallucinations had a pattern of onset at one day post completion of DMA administration and were associated with EEG changes. The lowest dose at which hallucinations were recognized was equivalent to 1.9 times that delivered in a conditioning regimen utilizing BUSULFEX 0.8 mg/kg every 6 hours x 16 doses. Other neurological toxicities included somnolence, lethargy, and confusion. The relative contribution of DMA and/or other concomitant medications to neurologic and hepatic toxicities observed with BUSULFEX is difficult to ascertain.

Treatment with BUSULFEX at the recommended dose and schedule will result in profound myelosuppression in 100% of patients, including granulocytopenia, thrombocytopenia, anemia, or a combined loss of formed elements of the blood.

Adverse reaction information is primarily derived from the clinical study (N=61) of BUSULFEX and the data obtained for high-dose oral busulfan conditioning in the setting of randomized, controlled trials identified through a literature review.

BUSULFEX Clinical Trials

In the BUSULFEX (busulfan) Injection allogeneic stem cell transplantation clinical trial, all patients were treated with BUSULFEX 0.8 mg/kg as a two-hour infusion every six hours for 16 doses over four days, combined with cyclophosphamide 60 mg/kg x 2 days. Ninety-three percent (93%) of evaluable patients receiving this dose of BUSULFEX maintained an AUC less than 1,500 µM•min for dose 9, which has generally been considered the level that minimizes the risk of HVOD.

Table 3: Summary of the Incidence (≥20%) of Non-Hematologic Adverse Events through BMT Day +28 in Patients who Received BUSULFEX Prior to Allogeneic Hematopoietic Progenitor Cell Transplantation
Non-Hematological Adverse Events* | Percent Incidence
BODY AS A WHOLE
Fever | 80
Headache | 69
Asthenia | 51
Chills | 46
Pain | 44
Edema General | 28
Allergic Reaction | 26
Chest Pain | 26
Inflammation at Inj Site | 25
Pain Back | 23
CARDIOVASCULAR SYSTEM
Tachycardia | 44
Hypertension | 36
Thrombosis | 33
Vasodilation | 25
DIGESTIVE SYSTEM
Nausea | 98
Stomatitis (Mucositis) | 97
Vomiting | 95
Anorexia | 85
Diarrhea | 84
Abdominal Pain | 72
Dyspepsia | 44
Constipation | 38
Dry Mouth | 26
Rectal Disorder | 25
Abdominal Enlargement | 23
METABOLIC AND NUTRITIONAL SYSTEM
Hypomagnesemia | 77
Hyperglycemia | 66
Hypokalemia | 64
Hypocalcemia | 49
Hyperbilirubinemia | 49
Edema | 36
SGPT Elevation | 31
Creatinine Increased | 21
NERVOUS SYSTEM
Insomnia | 84
Anxiety | 72
Dizziness | 30
Depression | 23
RESPIRATORY SYSTEM
Rhinitis | 44
Lung Disorder | 34
Cough | 28
Epistaxis | 25
Dyspnea | 25
SKIN AND APPENDAGES
Rash | 57
Pruritus | 28
*Includes all reported adverse events regardless of severity (toxicity grades 1-4)

The following sections describe clinically significant events occurring in the BUSULFEX clinical trials, regardless of drug attribution. For pediatric information, see Special Populations – Pediatric section.

Hematologic:At the indicated dose and schedule, BUSULFEX produced profound myelosuppression in 100% of patients. Following hematopoietic progenitor cell infusion, recovery of neutrophil counts to ≥500 cells/mm^3 occurred at median day 13 when prophylactic G-CSF was administered to the majority of participants on the study. The median number of platelet transfusions per patient on study was 6, and the median number of red blood cell transfusions on study was 4. Prolonged prothrombin time was reported in one patient (2%).

Gastrointestinal:Gastrointestinal toxicities were frequent and generally considered to be related to the drug. Few were categorized as serious. Mild or moderate nausea occurred in 92% of patients in the allogeneic clinical trial, and mild or moderate vomiting occurred in 95% through BMT Day +28; nausea was severe in 7%. The incidence of vomiting during BUSULFEX administration (BMT Day –7 to –4) was 43% in the allogeneic clinical trial. Grade 3-4 stomatitis developed in 26% of the participants, and grade 3 esophagitis developed in 2%. Grade 3-4 diarrhea was reported in 5% of the allogeneic study participants, while mild or moderate diarrhea occurred in 75%. Mild or moderate constipation occurred in 38% of patients; ileus developed in 8% and was severe in 2%. Forty-four percent (44%) of patients reported mild or moderate dyspepsia. Two percent (2%) of patients experienced mild hematemesis. Pancreatitis developed in 2% of patients. Mild or moderate rectal discomfort occurred in 24% of patients. Severe anorexia occurred in 21% of patients and was mild/moderate in 64%.

Hepatic:Hyperbilirubinemia occurred in 49% of patients in the allogeneic BMT trial. Grade 3/4 hyperbilirubinemia occurred in 30% of patients within 28 days of transplantation and was considered lifethreatening in 5% of these patients. Hyperbilirubinemia was associated with graft-versus-host disease in six patients and with hepatic veno-occlusive disease in 5 patients. Grade 3/4 SGPT elevations occurred in 7% of patients. Alkaline phosphatase increases were mild or moderate in 15% of patients. Mild or moderate jaundice developed in 12% of patients, and mild or moderate hepatomegaly developed in 6%.

Hepatic veno-occlusive disease:Hepatic veno-occlusive disease (HVOD) is a recognized potential complication of conditioning therapy prior to transplant. Based on clinical examination and laboratory findings, hepatic veno-occlusive disease was diagnosed in 8% (5/61) of patients treated with BUSULFEX in the setting of allogeneic transplantation, was fatal in 2/5 cases (40%), and yielded an overall mortality from HVOD in the entire study population of 2/61 (3%). Three of the five patients diagnosed with HVOD were retrospectively found to meet the Jones’ criteria.

Graft-versus-host disease:Graft-versus-host disease developed in 18% of patients (11/61) receiving allogeneic transplants; it was severe in 3%, and mild or moderate in 15%. There were 3 deaths (5%) attributed to GVHD.

Edema:Patients receiving allogeneic transplant exhibited some form of edema (79%), hypervolemia, or documented weight increase (8%); all events were reported as mild or moderate.

Infection/Fever:Fifty-one percent (51%) of patients experienced one or more episodes of infection. Pneumonia was fatal in one patient (2%) and life-threatening in 3% of patients. Fever was reported in 80% of patients; it was mild or moderate in 78% and severe in 3%. Forty-six percent (46%) of patients experienced chills.

Cardiovascular:Mild or moderate tachycardia was reported in 44% of patients. In 7 patients (11%) it was first reported during BUSULFEX administration. Other rhythm abnormalities, which were all mild or moderate, included arrhythmia (5%), atrial fibrillation (2%), ventricular extrasystoles (2%), and third degree heart block (2%). Mild or moderate thrombosis occurred in 33% of patients, and all episodes were associated with the central venous catheter. Hypertension was reported in 36% of patients and was Grade 3/4 in 7%. Hypotension occurred in 11% of patients and was Grade 3/4 in 3%. Mild vasodilation (flushing and hot flashes) was reported in 25% of patients. Other cardiovascular events included cardiomegaly (5%), mild ECG abnormality (2%), grade 3/4 left-sided heart failure in one patient (2%), and moderate pericardial effusion (2%). These events were reported primarily in the post-cyclophosphamide phase.

Pulmonary:Mild or moderate dyspnea occurred in 25% of patients and was severe in 2%. One patient (2%) experienced severe hyperventilation; and in 2 (3%) additional patients it was mild or moderate. Mild rhinitis and mild or moderate cough were reported in 44% and 28% of patients, respectively. Mild epistaxis events were reported in 25%. Three patients (5%) on the allogeneic study developed documented alveolar hemorrhage. All required mechanical ventilatory support and all died. Non-specific interstitial fibrosis was found on wedge biopsies performed with video assisted thoracoscopy in one patient on the allogeneic study who subsequently died from respiratory failure on BMT Day +98. Other pulmonary events, reported as mild or moderate, included pharyngitis (18%), hiccup (18%), asthma (8%), atelectasis (2%), pleural effusion (3%), hypoxia (2%), hemoptysis (3%), and sinusitis (3%).

Neurologic:The most commonly reported adverse events of the central nervous system were insomnia (84%), anxiety (75%), dizziness (30%), and depression (23%). Severity was mild or moderate except for one patient (1%) who experienced severe insomnia. One patient (1%) developed a life-threatening cerebral hemorrhage and a coma as a terminal event following multi-organ failure after HVOD. Other events considered severe included delirium (2%), agitation (2%), and encephalopathy (2%). The overall incidence of confusion was 11%, and 5% of patients were reported to have experienced hallucinations. The patient who developed delirium and hallucination on the allogeneic study had onset of confusion at the completion of BUSULFEX (busulfan) Injection. The overall incidence of lethargy in the allogeneic BUSULFEX clinical trial was 7%, and somnolence was reported in 2%. One patient (2%) treated in an autologous transplantation study experienced a seizure while receiving cyclophosphamide, despite prophylactic treatment with phenytoin.

Renal:Creatinine was mildly or moderately elevated in 21% of patients. BUN was increased in 3% of patients and to a grade 3/4 level in 2%. Seven percent of patients experienced dysuria, 15% oliguria, and 8% hematuria. There were 4 (7%) Grade 3/4 cases of hemorrhagic cystitis in the allogeneic clinical trial.

Skin:Rash (57%) and pruritus (28%) were reported; both conditions were predominantly mild. Alopecia was mild in 15% of patients and moderate in 2%. Mild vesicular rash was reported in 10% of patients and mild or moderate maculopapular rash in 8%. Vesiculo-bullous rash was reported in 10%, and exfoliative dermatitis in 5%. Erythema nodosum was reported in 2%, acne in 7%, and skin discoloration in 8%.

Metabolic:Hyperglycemia was observed in 67% of patients and Grade 3/4 hyperglycemia was reported in 15%. Hypomagnesemia was mild or moderate in 77% of patients; hypokalemia was mild or moderate in 62% and severe in 2%; hypocalcemia was mild or moderate in 46% and severe in 3%; hypophosphatemia was mild or moderate in 17%; and hyponatremia was reported in 2%.

Other:Other reported events included headache (mild or moderate 64%, severe 5%), abdominal pain (mild or moderate 69%, severe 3%), asthenia (mild or moderate 49%, severe 2%), unspecified pain (mild or moderate 43%, severe 2%), allergic reaction (mild or moderate 24%, severe 2%), injection site inflammation (mild or moderate 25%), injection site pain (mild or moderate 15%), chest pain (mild or moderate 26%), back pain (mild or moderate 23%), myalgia (mild or moderate 16%), arthralgia (mild or moderate 13%), and ear disorder in 3%.

Deaths:There were two deaths through BMT Day +28 in the allogeneic transplant setting. There were an additional six deaths BMT Day +29 through BMT Day +100 in the allogeneic transplant setting.

Oral Busulfan Literature Review.A literature review identified four randomized, controlled trials that evaluated a high-dose oral busulfan-containing conditioning regimen for allogeneic bone marrow transplantation in the setting of CML (see CLINICAL STUDIES). The safety outcomes reported in those trials are summarized in Table 4 below for a mixed population of hematological malignancies (AML, CML, and ALL).

Table 4: Summary of safety analyses from the randomized, controlled trials utilizing a high dose oral busulfan-containing conditioning regimen that were identified in a literature review.
Clift
CML Chronic Phase
TRM* | VOD** | GVHD*** | Pulmonary | Hemorrhagic | Seizure
 |  |  |  | Cystitis
Death | No Report | Acute ≥ Grade 2 | 1 death from | No Report | No Report
≤100d |  | =35% | Idiopathic
=4.1% |  | Chronic =41% | Interstitial
(3/73) |  | (30/73) | Pneumonitis
 |  |  | and
 |  |  | 1 death from
 |  |  | Pulmonary
 |  |  | Fibrosis
Devergie
CML Chronic Phase
TRM | VOD | GVHD | Pulmonary | Hemorrhagic | Seizure
 |  |  |  | Cystitis
38% | 7.7% (5/65) | Acute ≥ Grade 2 | Interstitial | 10.8% (7/65) | No report
 | Deaths=4.6% | =41% | Pneumonitis=
 | (3/65) | (24/59 at risk) | 16.9% (11/65)
Ringden
CML, AML, ALL
TRM | VOD | GVHD | Pulmonary | Hemorrhagic | Seizure
 |  |  |  | Cystitis
28% | 12% | Acute ≥ Grade 2 | Interstitial | 24% | 6%
 |  | GVHD=26% | Pneumonitis
 |  | Chronic GVHD | =14%
 |  | =45%
Blume
CML, AML, ALL
TRM | VOD | GVHD | Pulmonary | Hemorrhagic | Seizure
 |  |  |  | Cystitis
No Report | Deaths | Acute ≥ Grade 2 | No Report | No Report | No Report
 | =4.9% | GVHD=22%
 |  | (13/58 at risk)
 |  | Chronic GVHD
 |  | =31%
 |  | (14/45 at risk)
*TRM = Transplantation Related Mortality
**VOD = Veno-Occlusive Disease of the liver
***GVHD = Graft versus Host Disease

OVERDOSAGE

There is no known antidote to BUSULFEX other than hematopoietic progenitor cell transplantation. In the absence of hematopoietic progenitor cell transplantation, the recommended dosage for BUSULFEX would constitute an overdose of busulfan. The principal toxic effect is profound bone marrow hypoplasia/aplasia and pancytopenia, but the central nervous system, liver, lungs, and gastro intestinal tract may be affected. The hematologic status should be closely monitored and vigorous supportive measures instituted as medically indicated. Survival after a single 140 mg dose of Myleran® Tablets in an 18 kg, 4-year old child has been reported. Inadvertent administration of a greater than normal dose of oral busulfan (2.1 mg/kg; total dose of 23.3 mg/kg) occurred in a 2-year old child prior to a scheduled bone marrow transplant without sequelae. An acute dose of 2.4 g was fatal in a 10-year old boy. There is one report that busulfan is dialyzable, thus dialysis should be considered in the case of overdose. Busulfan is metabolized by conjugation with glutathione, thus administration of glutathione may be considered.

DOSAGE AND ADMINISTRATION

When BUSULFEX (busulfan) Injection is administered as a component of the BuCy conditioning regimen prior to bone marrow or peripheral blood progenitor cell replacement, the recommended doses are as follows:

Adults (BuCy2):The usual adult dose is 0.8 mg/kg of ideal body weight or actual body weight, whichever is lower, administered every six hours for four days (a total of 16 doses). For obese, or severely obese patients, BUSULFEX should be administered based on adjusted ideal body weight. Ideal body weight (IBW) should be calculated as follows (height in cm, and weight in kg): IBW (kg; men)= 50 + 0.91x (height in cm -152); IBW (kg; women)= 45 + 0.91x (height in cm - 152). Adjusted ideal body weight (AIBW) should be calculated as follows: AIBW= IBW + 0.25x (actual weight -IBW). Cyclophosphamide is given on each of two days as a one-hour infusion at a dose of 60 mg/kg beginning on BMT day –3, no sooner than six hours following the 16 th dose of BUSULFEX.

BUSULFEX clearance is best predicted when the BUSULFEX dose is administered based on adjusted ideal body weight. Dosing BUSULFEX based on actual body weight, ideal body weight or other factors can produce significant differences in BUSULFEX (busulfan) Injection clearance among lean, normal and obese patients.

BUSULFEX should be administered intravenously via a central venous catheter as a two-hour infusion every six hours for four consecutive days for a total of 16 doses. All patients should be premedicated with phenytoin as busulfan is known to cross the blood brain barrier and induce seizures. Phenytoin reduces busulfan plasma AUC by 15%. Use of other anticonvulsants may result in higher busulfan plasma AUCs, and an increased risk of VOD or seizures. In cases where other anticonvulsants must be used, plasma busulfan exposure should be monitored (See DRUG INTERACTIONS). Antiemetics should be administered prior to the first dose of BUSULFEX and continued on a fixed schedule through administration of BUSULFEX. Where available, pharmacokinetic monitoring may be considered to further optimize therapeutic targeting.

Pediatrics:The effectiveness of BUSULFEX in the treatment of CML has not been specifically studied in pediatric patients. For additional information see Special Populations -Pediatric section.

Preparation and Administration Precautions:

An administration set with minimal residual hold-up volume (2-5 cc) should be used for product administration.

As with other cytotoxic compounds, caution should be exercised in handling and preparing the solution of BUSULFEX. Skin reactions may occur with accidental exposure. The use of gloves is recommended. If BUSULFEX or diluted BUSULFEX solution contacts the skin or mucosa, wash the skin or mucosa thoroughly with water. BUSULFEX is a clear, colorless solution. Parenteral drug products should be visually inspected for particulate matter and discoloration prior to administration whenever the solution and container permit. If particulate matter is seen in the BUSULFEX ampoule the drug should not be used.

Preparation for Intravenous Administration:

BUSULFEX must be diluted prior to use with either 0.9% Sodium Chloride Injection, USP (normal saline) or 5% Dextrose Injection, USP (D5W). The diluent quantity should be 10 times the volume of BUSULFEX, so that the final concentration of busulfan is approximately 0.5 mg/mL. Calculation of the dose for a 70 kg patient, would be performed as follows:

(70kg patient) x (0.8 mg/kg) ÷ (6 mg/mL) = 9.3 mL BUSULFEX (56 mg total dose).

To prepare the final solution for infusion, add 9.3 mL of BUSULFEX to 93 mL of diluent (normal saline or D5W) as calculated below:

(9.3 mL BUSULFEX)x(10)=93 mL of either diluent plus the 9.3 mL of BUSULFEX to yield a final concentration of busulfan of 0.54 mg/mL (9.3 mL x 6 mg/mL ÷ 102.3 mL = 0.54 mg/mL).

All transfer procedures require strict adherence to aseptic techniques, preferably employing a vertical laminar flow safety hood while wearing gloves and protective clothing.

DO NOT put the BUSULFEX into an intravenous bag or large-volume syringe that does not contain normal saline or D5W. Always add the BUSULFEX to the diluent, not the diluent to the BUSULFEX. Mix thoroughly by inverting several times. DO NOT USE POLYCARBONATE SYRINGES OR POLYCARBONATE FILTER NEEDLES WITH BUSULFEX.

Infusion pumps should be used to administer the diluted BUSULFEX solution. Set the flow rate of the pump to deliver the entire prescribed BUSULFEX dose over two hours. Prior to and following each infusion, flush the indwelling catheter line with approximately 5mL of 0.9% Sodium Chloride Injection, USP or 5% Dextrose Injection, USP. DO NOT infuse concomitantly with another intravenous solution of unknown compatibility. WARNING: RAPID INFUSION OF BUSULFEX HAS NOT BEEN TESTED AND IS NOT RECOMMENDED.

STABILITY

Unopened vials of BUSULFEX are stable until the date indicated on the package when stored under refrigeration at 2°-8°C (36°-46°F).

BUSULFEX diluted in 0.9% Sodium Chloride Injection, USP or 5% Dextrose Injection, USP is stable at room temperature (25°C) for up to 8 hours but the infusion must be completed within that time. BUSULFEX diluted in 0.9% Sodium Chloride Injection, USP is stable at refrigerated conditions (2°-8°C) for up to 12 hours but the infusion must be completed within that time.

HOW SUPPLIED

BUSULFEX is supplied as a sterile solution in 10 mL single-use clear glass vials each containing 60 mg of busulfan at a concentration of 6 mg/mL for intravenous use.

NDC 67286-0054-2 10mL (6mg/mL) in packages of eight vials.

Unopened vials of BUSULFEX must be stored under refrigerated conditions between 2°-8°C (36°-46°F).

HANDLING AND DISPOSAL

Procedures for proper handling and disposal of anticancer drugs should be considered. Several guidelines on this subject have been published.^1,2,3,4,5,6 There is no general agreement that all of the procedures recommended in the guidelines are necessary or appropriate.

Marketed by:

PDL BioPharma, Inc.

Redwood City, CA 94063

Manufactured by:

Ben Venue Labs, Inc.

Bedford OH 44146

United States Patent numbers are 5,430,057 and 5,559,148. Canadian Patent number is CA2171738. European Union Patent number is EP 0 725 637 B1.

Part No. 131401

Rev Date: April 2007

References

1. Recommendations for the safe handling of parenteral antineoplastic drugs. Washington , DC: Division of Safety, National Institutes of Health; 1983. US Department of Health and Human Services, Public Health Service publication NIH 83-2621.
2. AMA Council on Scientific Affairs. Guidelines for handling parenteral antineoplastics. JAMA 1985; 253:1590-1591.
3. National Study Commission on Cytotoxic Exposure. Recommendations for handling cytotoxic agents. 1987. Available from Louis P. Jeffrey, Chairman, National Study Commission on Cytotoxic Exposure. Massachusetts College of Pharmacy and Allied Health Sciences, 179 Longhwood Avenue , Boston , MA 02115.
4. Clinical Oncology Society of Australia. Guidelines and recommendations for safe handling of antineoplastic agents. Med J Australia 1983; 1:426-428.
5. Jones RB, Frank R, Mass T. Safe handling of chemotherapeutic agents: a report from the Mount Sinai Medical Center. CA-A Cancer J for Clin 1983; 33:258-263.
6. American Society of Hospital Pharmacists. ASHP technical assistance bulletin on handling cytotoxic and hazardous drugs. Am J Hosp Pharm 1990; 47:1033-1049.

For questions of medical nature call 1-866-437-7742 or 510-574-1444 (int’l)